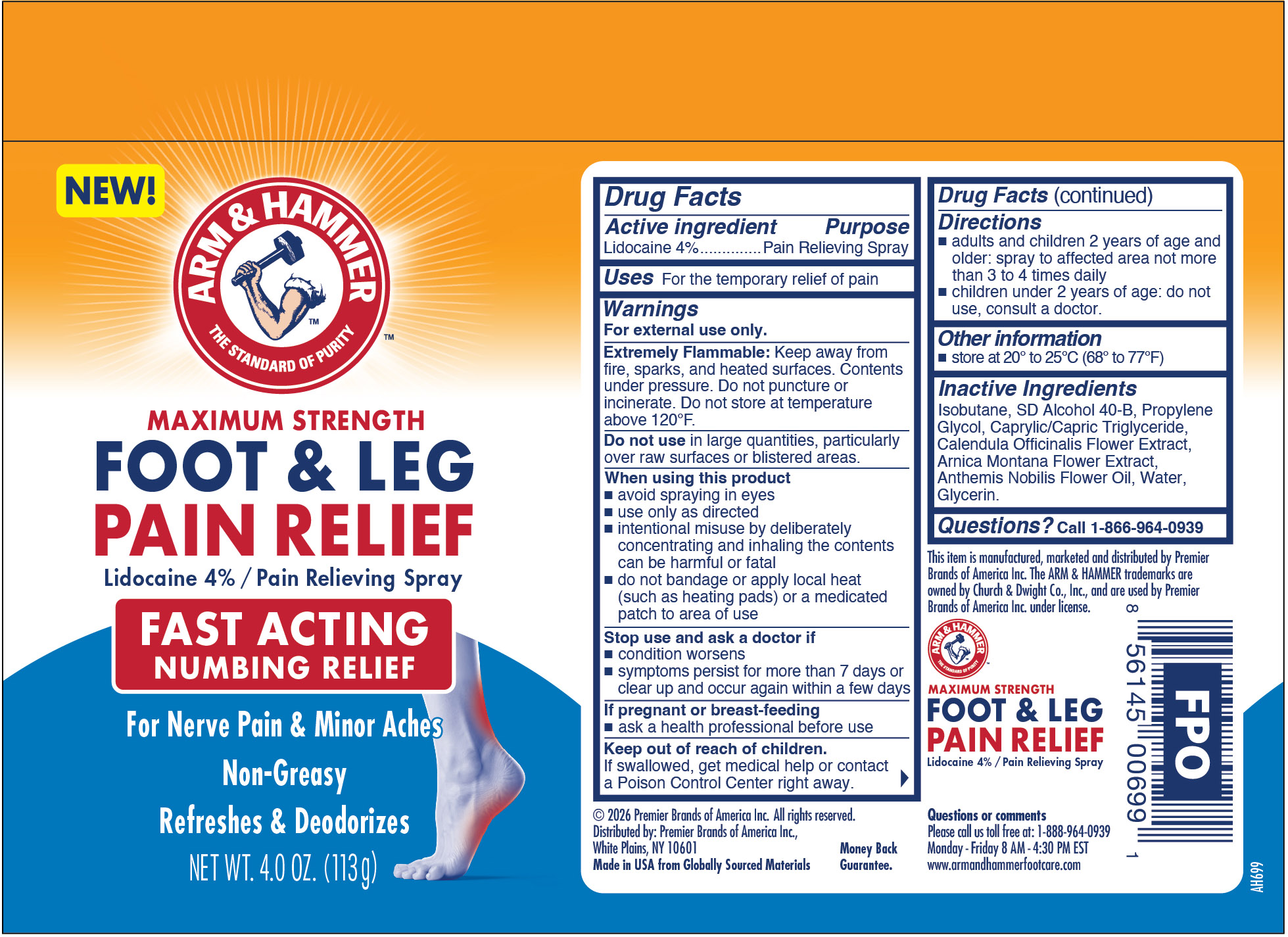 DRUG LABEL: Foot and Leg Pain Relief
NDC: 56104-007 | Form: AEROSOL, SPRAY
Manufacturer: Premier Brands of America Inc.
Category: otc | Type: HUMAN OTC DRUG LABEL
Date: 20251106

ACTIVE INGREDIENTS: LIDOCAINE 40 mg/1 g
INACTIVE INGREDIENTS: ISOBUTANE; ALCOHOL; PROPYLENE GLYCOL; CAPRYLIC/CAPRIC TRIGLYCERIDE; CALENDULA OFFICINALIS FLOWER; ARNICA MONTANA FLOWER WATER; ANTHEMIS NOBILIS FLOWER OIL; WATER; GLYCERIN

Arm & Hammer Foot & Leg Pain Relief Spray

Active Ingredients

Lidocaine 4%

Purpose

Pain Relieving Spray

Uses

For the temporary relief of pain

Warnings

For external use only.

Extremely Flammable:

Keep away from fire, sparks, and heated surfaces. Contents under pressure. Do not puncture or incinerate. Do not store at temperature above 120ºF.

Do not use

in large quantities, particularly over raw surfaces or blistered areas.

When using this product

- avoid spraying in eyes
- use only as directed
- intentional misuse by deliberately concentrating and inhaling the contents can be harmful or fatal
- do not bandage or apply local heat (such as heating pads) or a medicated patch to area of use

Stop use and ask a doctor if

- condition worsens
- symptoms persist for more than 7 days or clear up and occur again within a few days

If pregnant or breast-feeding

- ask a health professional before use

Keep out of reach of children.

If swallowed, get medical help or contact a Poison Control Center right away.

Directions

- adults and children 2 years of age and older: spray to affected area not more than 3 to 4 times daily
- children under 2 years of age: do not use, consult a doctor.

Other information

store between 20º to 25ºC (68º to 77ºF)

Inactive ingredients

Isobutane, SD Alcohol 40-B, Propylene Glycol, Caprylic/Capric Triglyceride,Calendula Officinalis Flower Extract, Arnica Montana Flower Extract, Anthemis Nobilis Flower Oil, Water, Glycerin.

Questions?

Call 1-866-964-0939

RECENT MAJOR CHANGES

..

Principal Display Panel

ARM & HAMMER

MAXIMUM STRENGTH

FOOT & LEG

PAIN RELIEF

Lidocaine 4% / Pain Relieving Spray

FAST ACTING

NUMBING RELIEF

For Nerve Pain & Minor Aches

Non-Greasy

Refreshes & Deodorizes

NET WT. 4.0 OZ. (113g)